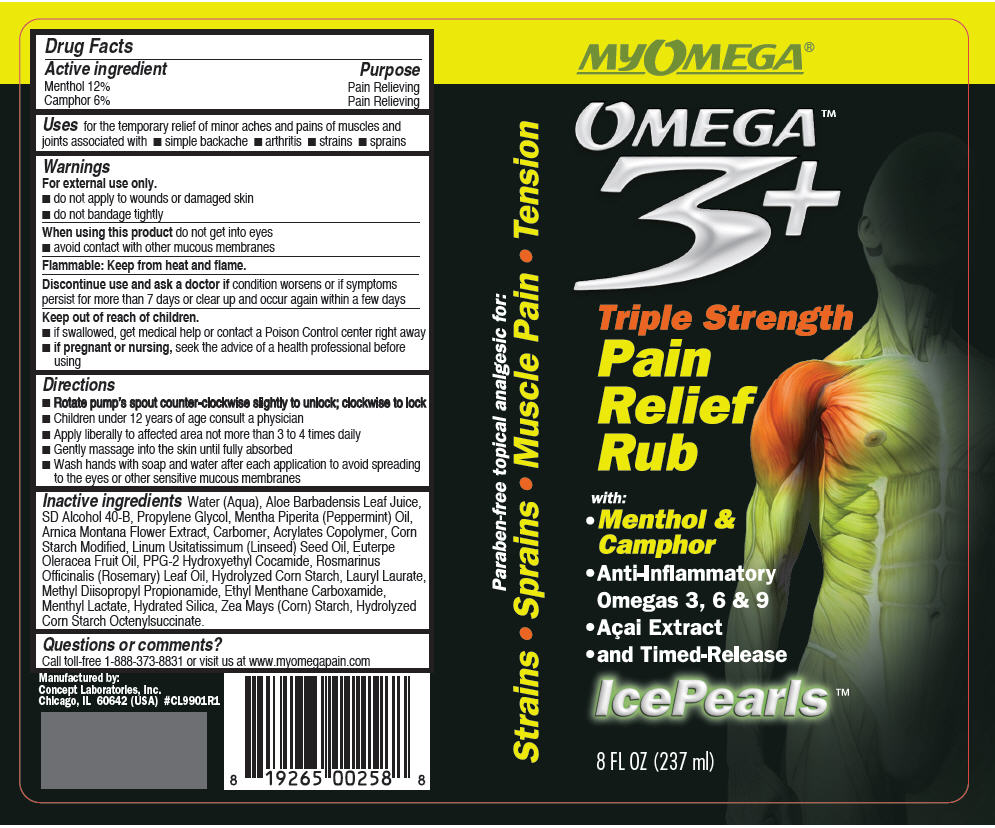 DRUG LABEL: My Omega 3 
NDC: 64058-345 | Form: CREAM
Manufacturer: Concept Laboratories, Inc.
Category: otc | Type: HUMAN OTC DRUG LABEL
Date: 20160913

ACTIVE INGREDIENTS: MENTHOL, UNSPECIFIED FORM 0.12 g/1 g; CAMPHOR (SYNTHETIC) 0.06 g/1 g
INACTIVE INGREDIENTS: Water; ALOE VERA LEAF; PROPYLENE GLYCOL; PEPPERMINT OIL; ALCOHOL; STARCH, CORN; ARNICA MONTANA FLOWER; LINSEED OIL; ROSEMARY OIL; ACAI OIL; PPG-2 HYDROXYETHYL COCAMIDE; METHYL DIISOPROPYL PROPIONAMIDE; ETHYL MENTHANE CARBOXAMIDE; MENTHYL LACTATE, (-)-; LAURYL LAURATE; HYDRATED SILICA

My Omega® 3
Rub

Drug Facts

ACTIVE INGREDIENT

Active ingredient | Purpose
Menthol 12% | Pain Relieving
Camphor 6% | Pain Relieving

Uses

for the temporary relief of minor aches and pains of muscles and joints associated with

- simple backache
- arthritis
- strains
- sprains

Warnings

For external use only.

- do not apply to wounds or damaged skin
- do not bandage tightly

When using this product do not get into eyes

- avoid contact with other mucous membranes

Flammable

Keep from heat and flame.

STOP USE

Discontinue use and ask a doctor if condition worsens or if symptoms persist for more than 7 days or clear up and occur again within a few days

Keep out of reach of children.

- if swallowed, get medical help or contact a Poison Control center right away

PREGNANCY OR BREAST FEEDING

- if pregnant or nursing, seek the advice of a health professional before using

Directions

- Rotate pump's spout counter-clockwise slightly to unlock; clockwise to lock
- Children under 12 years of age consult a physician
- Apply liberally to affected area not more than 3 to 4 times daily
- Gently massage into the skin until fully absorbed
- Wash hands with soap and water after each application to avoid spreading to the eyes or other sensitive mucous membranes

Inactive ingredients

Water (Aqua), Aloe Barbadensis Leaf Juice, SD Alcohol 40-B, Propylene Glycol, Mentha Piperita (Peppermint) Oil, Arnica Montana Flower Extract, Carbomer, Acrylates Copolymer, Corn Starch Modified, Linum Usitatissimum (Linseed) Seed Oil, Euterpe Oleracea Fruit Oil, PPG-2 Hydroxyethyl Cocamide, Rosmarinus Officinalis (Rosemary) Leaf Oil, Hydrolyzed Corn Starch, Lauryl Laurate, Methyl Diisopropyl Propionamide, Ethyl Menthane Carboxamide, Menthyl Lactate, Hydrated Silica, Zea Mays (Corn) Starch, Hydrolyzed Corn Starch Octenylsuccinate.

Questions or comments?

Call toll-free 1-888-373-8831 or visit us at www.myomegapain.com

Manufactured by:
Concept Laboratories, Inc.
Chicago, IL 60642

PRINCIPAL DISPLAY PANEL - 237 ml Bottle Label

MYOMEGA®

OMEGA™
3^+

Triple Strength
Pain
Relief
Rub

with:

- Menthol &
  Camphor
- Anti-Inflammatory
  Omegas 3, 6 & 9
- Açai Extract
- and Timed-Release

IcePearls ™

8 FL OZ (237 ml)

Paraben-free topical analgesic for:
Strains • Sprains • Muscle Pain • Tension